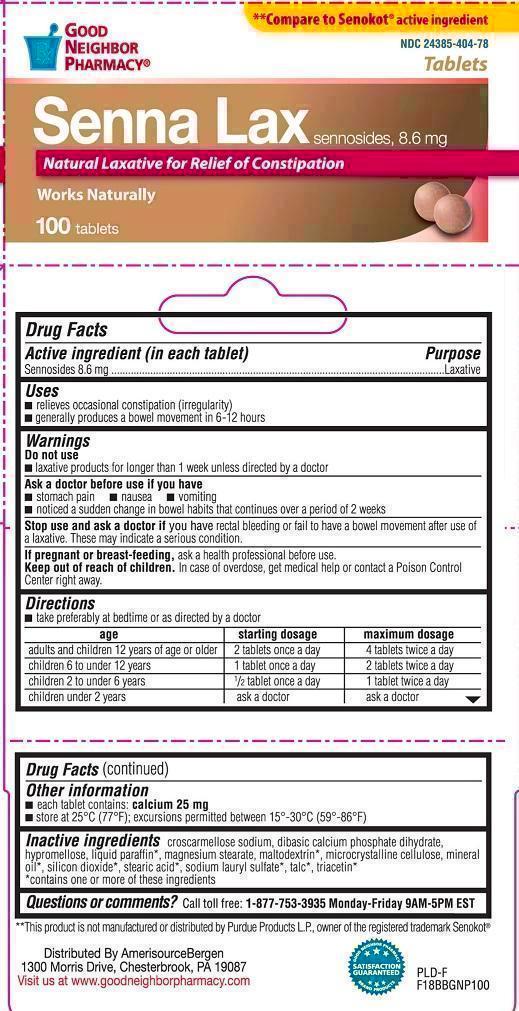 DRUG LABEL: Good Neighbor Senna
NDC: 24385-404 | Form: TABLET
Manufacturer: AmerisourceBergen
Category: otc | Type: HUMAN OTC DRUG LABEL
Date: 20121116

ACTIVE INGREDIENTS: SENNOSIDES A AND B 8.6 mg/1 1
INACTIVE INGREDIENTS: CROSCARMELLOSE SODIUM; CALCIUM PHOSPHATE, DIBASIC, DIHYDRATE; HYPROMELLOSES; PARAFFIN; MAGNESIUM STEARATE; MALTODEXTRIN; CELLULOSE, MICROCRYSTALLINE; MINERAL OIL; SILICON DIOXIDE; STEARIC ACID; SODIUM LAURYL SULFATE; TALC; TRIACETIN

Good Neighbor Senna Laxative

Active Ingredient

Sennosides 8.6 mg

Purpose

Laxative

Uses:

Relieves occasional constipation (irregularity)

Generally produces a bowel movement in 6 - 12 hours

Do not use Laxative products for longer than 1 week, unless directed by a doctor

Ask a doctor befor use if you have

- stomach pain
- nausea
- vomiting
- noticed a sudden change in bowel habits that continues over a period of 2 weeks

Stop use and ask a doctor

if you have rectal bleeding or fail to have a bowel movement after use of a laxative. These may indicate a serious condition.

If pregnant or breast feeding

ask a health professional before use.

Keep out of reach of children.

In case of overdose, get medical help or contact a Poison Control Center right away.

Other Information

- each tablet contains: calcium 25 mg/tablet

- store at 25°C (77°F); excursions permitted between 15°-30°C (59°-86°F)
- do not use if imprinted safety seal under cap is broken or missing
- This product is not manufactured or distributed by Purdue Products L.P., owner of the registered trademark Senokot®

Directions

Take preferably at bedtime or as directed by a doctor.

Age | Starting Dosage | Maximum Dosage
adults and children 12 years of age or older | 2tablets once a day | 4 tablets twice a day
children 6 to under 6 years | 1 tablet once a day | 2 tablets twice a day
children 2 to under 6 years | 1/2 tablet once a day | 1 tablet twice a day
children under 2 years | ask a doctor | ask a doctor

Inactive Ingredients

Colloidal silicon dioxide, croscarmellose sodium, dibasic calcium phosphate dihydrate, *dicalcium phosphate anhydrous, hypermellose, maltodextrin, magnesium stearate, microcrystalline cellulose, *mineral oil, *polyethylene glycol (PEG), stearic acid, talc, triacetin.

*May also contain.

Other Information

each tablet contains calcium 25mg

store at 25C. excursions permitted between 15-30C (59-86F)

Questions or Comments?

Call toll free: 1877-753-3935 Monday-Friday 9AM - 5PM EST

This product is not manufactured or distributed by Purdue Products, L.P., owner of th registered trademark Senokot.

Proudly Distributed by

Valu Merchandisers, Co.

Kansas City, KS 66106

Product Labeling

Good Neighbor Pharmacy

Senna Lax Sennosides, 8.6mg

Natural Laxative for Relief of Constipation

Works naturally 100tablets